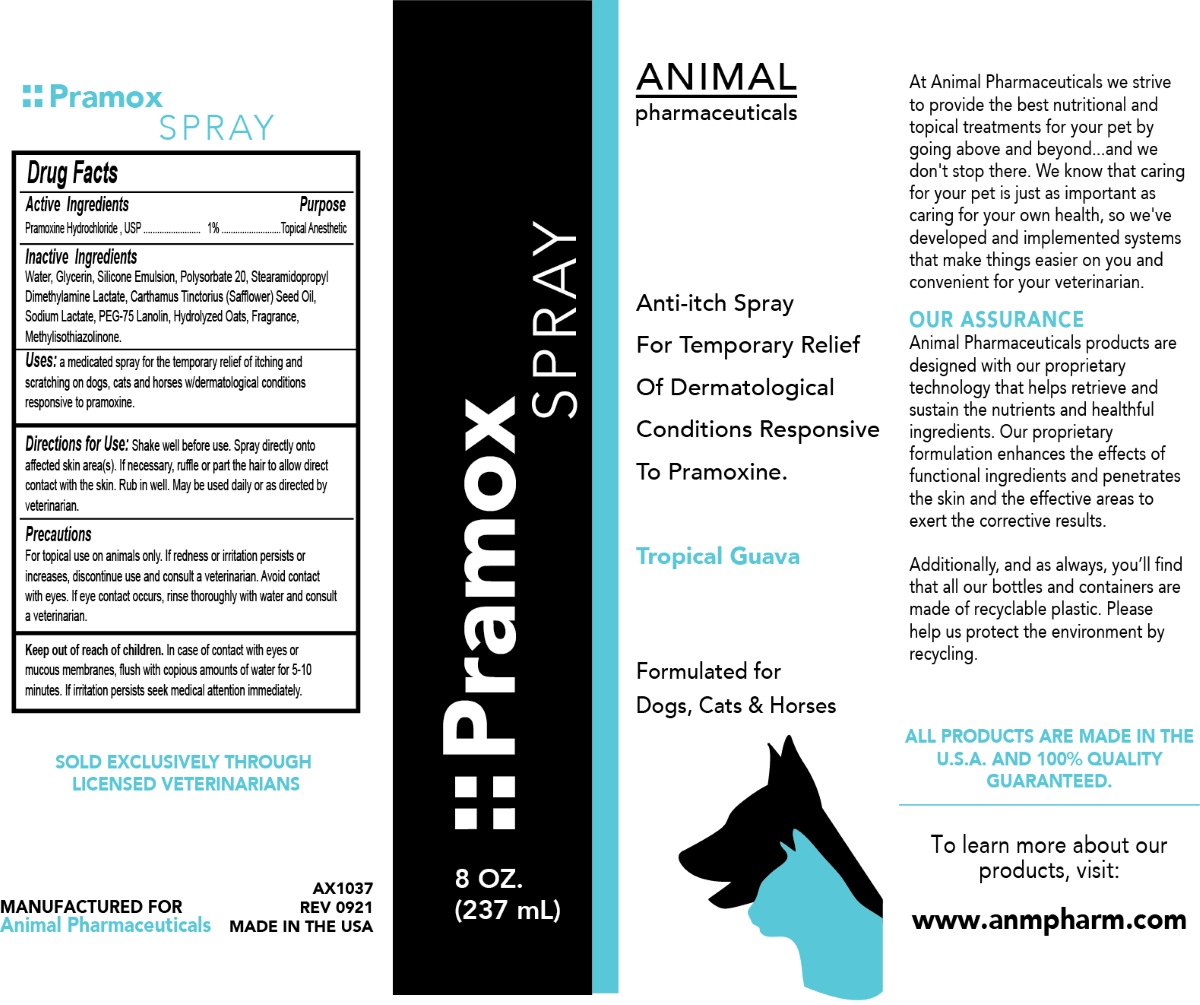 DRUG LABEL: Pramox
NDC: 68898-125 | Form: SPRAY
Manufacturer: Animal Pharmaceuticals
Category: animal | Type: OTC ANIMAL DRUG LABEL
Date: 20211018

ACTIVE INGREDIENTS: PRAMOXINE HYDROCHLORIDE 1 g/100 mL
INACTIVE INGREDIENTS: WATER; GLYCERIN; SILICON; POLYSORBATE 20; STEARAMIDOPROPYL DIMETHYLAMINE LACTATE; SAFFLOWER OIL; SODIUM LACTATE; PEG-75 LANOLIN; OAT; METHYLISOTHIAZOLINONE

Pramox SPRAY

Active Ingredients

Parmoxine Hydrochloride, USP 1%

Purpose

Topical Anesthetic

Inactive Ingredients

Water, Glycerin, Silicone Emulsion, Polysorbate 20, Stearamidopropyl Dimethylamine Lactate, Carthamus Tinctorius (Safflower) Seed Oil, Sodium Lactate, PEG-75 Lanolin, Hydrolyzed Oats, Fragrance, Methylisothiazolinone

Uses:

a medicated spray for the temporary relief of itching and scratching on dogs, cats and horses with dermatological conditions responsive to pramoxine.

Directions for Use:

Shake well before use. Spray directly onto affected skin area(s). If necessary, ruffle or part the hair to allow direct contact with the skin. Rub in well. May be used daily or as directed by veterinarian.

Precautions

For topical use on animals only. If redness or irritation persists or increases, discontinue use and consult a veterinarian. Avoid contact with eyes. If eye contact occurs, rinse thoroughly with water and consult a veterinarian.

Keep out of reach of children. In case of contact with eyes or mucous membranes, flush with copious amounts of water for 5-10 minutes. If irritation persists seek medical attention immediately.

Anti-itch Spray

For Temporary Relief Of Dermatological Conditions Responsive To Pramoxine.

Tropical Guava

Formulated for Dogs, Cats & Horses

At Animal Pharmaceuticals we strive to provide the best nutritional and topical treatments for your pet by going above and beyond....and we don't stop there. We know that caring for your pet is just as important as caring for your own health, so we've developed and implemented systems that make things easier on you and convenient for your veterinarian.

OUR ASSURANCE
Animal Pharmaceuticals products are designed with our proprietary technology that helps retrieve and sustain the nutrients and healthful ingredients. Our proprietary formulation enhances the effects of functional ingredients and penetrates the skin and the effective areas to exert the corrective results.

Additionally, and as always, you'll find that all our bottles and containers are made of recyclable plastic. Please help us protect the environment by recycling.

ALL PRODUCTS ARE MADE IN THE U.S.A. AND 100% QUALITY GUARANTEED.

To learn more about our products, visit:

www.anmpharm.com

SOLD EXCLUSIVELY THROUGH LICENSED VETERINARIANS

MANUFACTURED FOR
Animal Pharmaceuticals

MADE IN THE USA

PACKAGE LABEL

Packaging